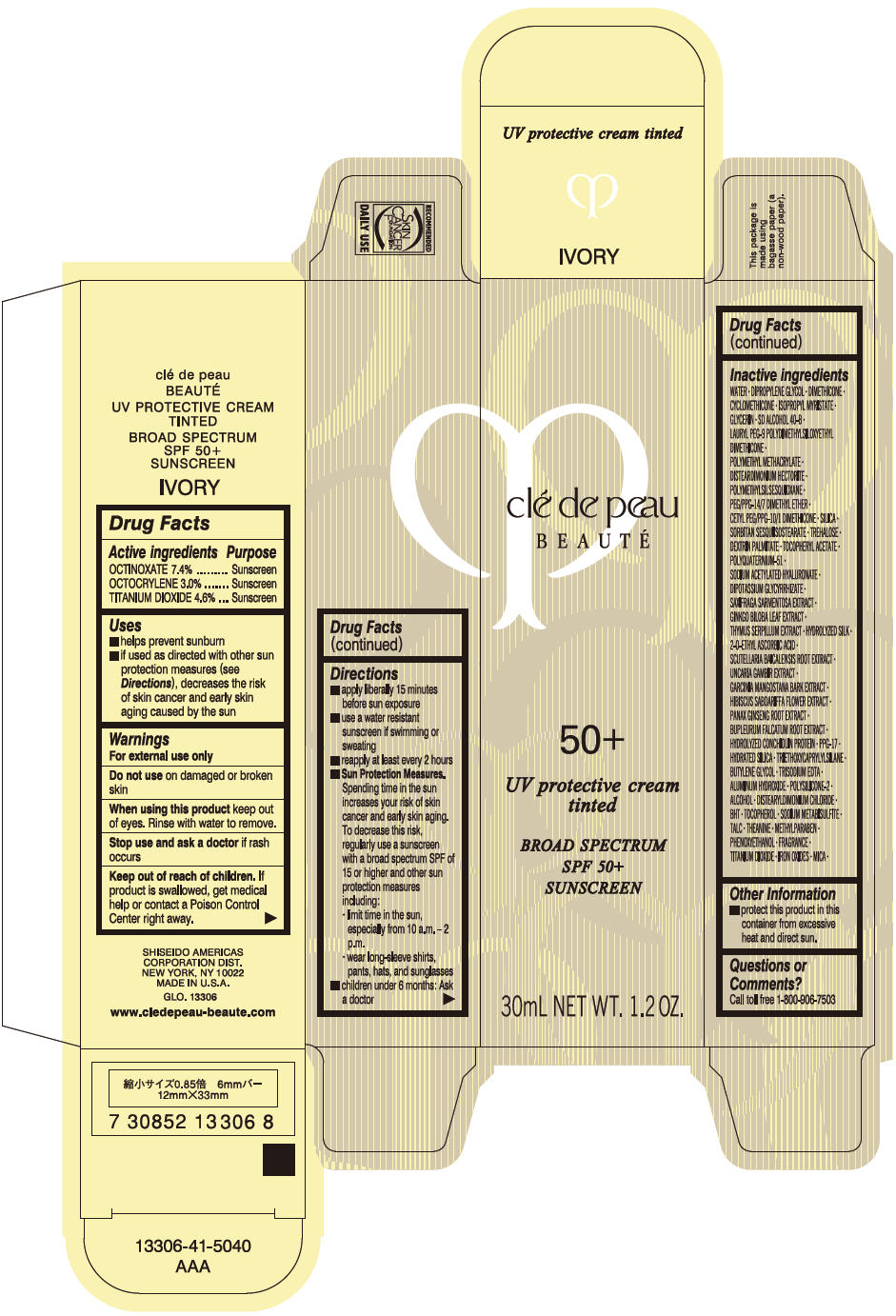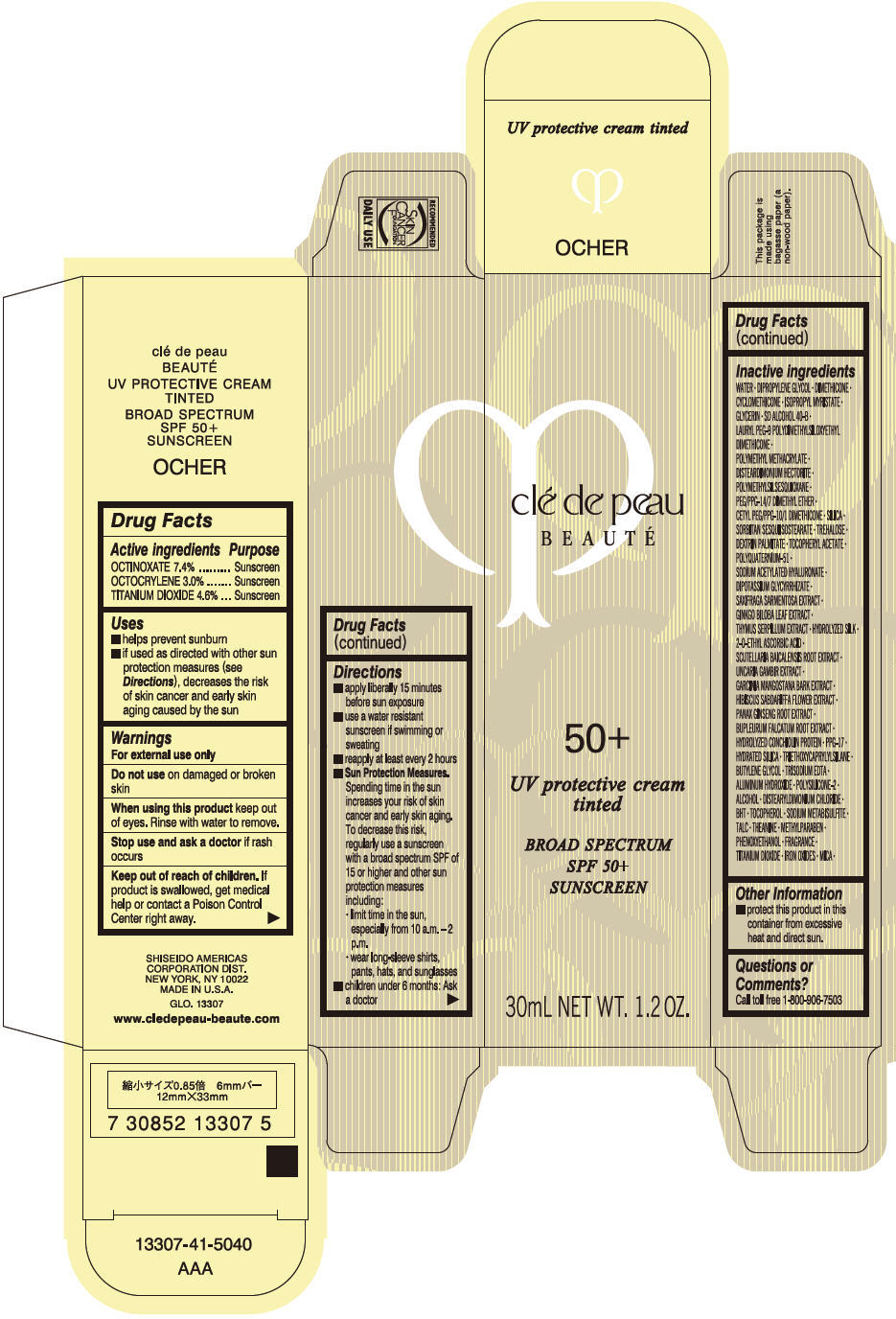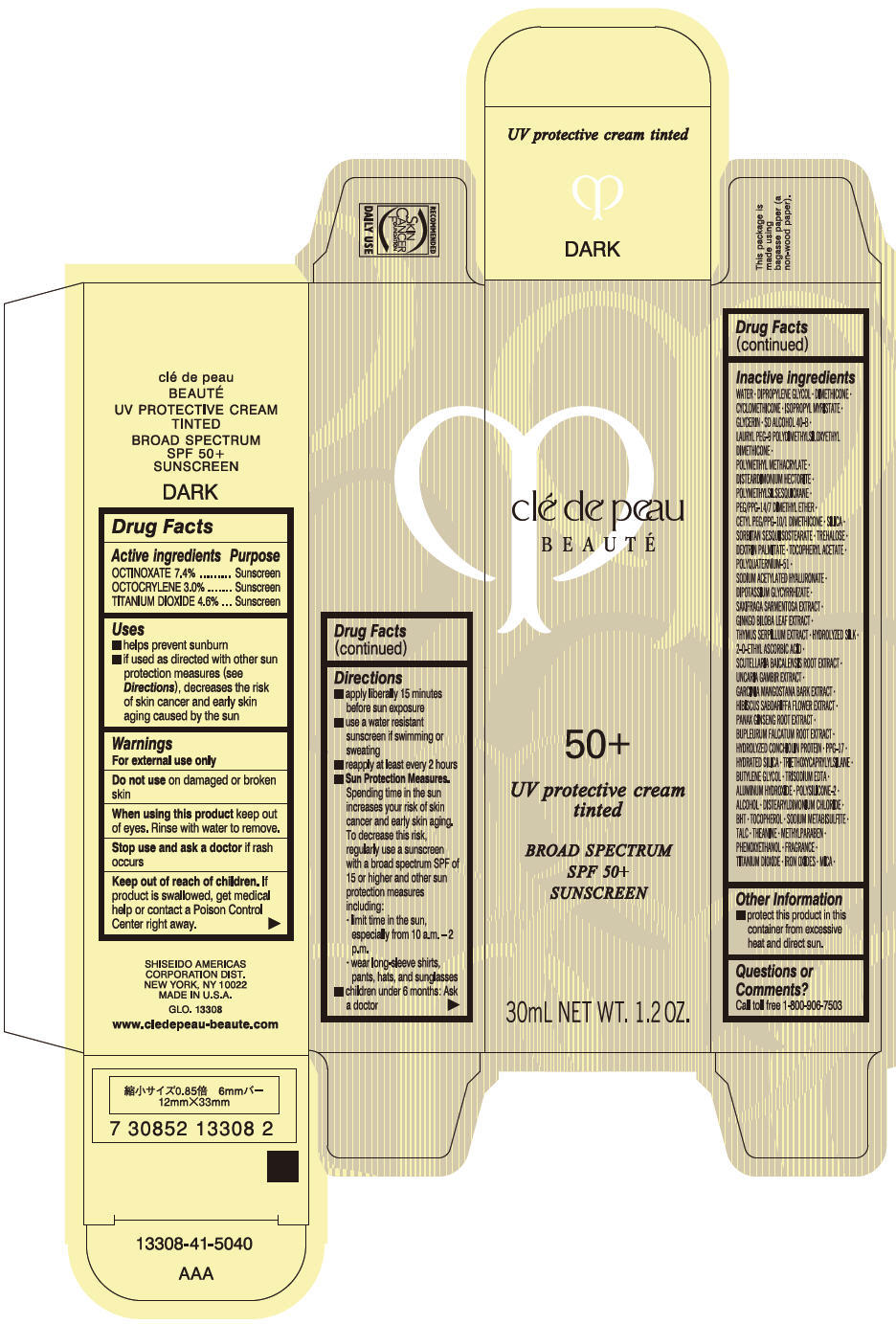 DRUG LABEL: CLE DE PEAU BEAUTE UV PROTECTIVE TINTED 

NDC: 58411-292 | Form: CREAM
Manufacturer: SHISEIDO AMERICAS CORPORATION
Category: otc | Type: HUMAN OTC DRUG LABEL
Date: 20181213

ACTIVE INGREDIENTS: OCTINOXATE 2449 mg/30 mL; OCTOCRYLENE 993 mg/30 mL; TITANIUM DIOXIDE 1522 mg/30 mL
INACTIVE INGREDIENTS: WATER; DIPROPYLENE GLYCOL; DIMETHICONE; ISOPROPYL MYRISTATE; GLYCERIN; CYCLOMETHICONE 5; LAURYL PEG-9 POLYDIMETHYLSILOXYETHYL DIMETHICONE; DISTEARDIMONIUM HECTORITE; POLYMETHYLSILSESQUIOXANE (4.5 MICRONS); PEG/PPG-14/7 DIMETHYL ETHER; CETYL PEG/PPG-10/1 DIMETHICONE (HLB 5); SILICON DIOXIDE; TREHALOSE; DEXTRIN PALMITATE (CORN; 20000 MW); .ALPHA.-TOCOPHEROL ACETATE, DL-; POLYQUATERNIUM-51 (2-METHACRYLOYLOXYETHYL PHOSPHORYLCHOLINE/N-BUTYL METHACRYLATE; 3:7); SODIUM ACETYLATED HYALURONATE; GLYCYRRHIZINATE DIPOTASSIUM; SAXIFRAGA STOLONIFERA LEAF; GINKGO; THYMUS SERPYLLUM; 2-O-ETHYL ASCORBIC ACID; SCUTELLARIA BAICALENSIS ROOT; GARCINIA MANGOSTANA BARK; HIBISCUS SABDARIFFA FLOWER; ASIAN GINSENG; BUPLEURUM FALCATUM ROOT; PPG-17; HYDRATED SILICA; TRIETHOXYCAPRYLYLSILANE; BUTYLENE GLYCOL; EDETATE TRISODIUM; ALUMINUM HYDROXIDE; ALCOHOL; DISTEARYLDIMONIUM CHLORIDE; BUTYLATED HYDROXYTOLUENE; .ALPHA.-TOCOPHEROL; SODIUM METABISULFITE; TALC; THEANINE; METHYLPARABEN; PHENOXYETHANOL; FERRIC OXIDE RED; FERRIC OXIDE YELLOW; FERROSOFERRIC OXIDE; MICA

CLÉ DE PEAU BEAUTÉ UV PROTECTIVE TINTED

Drug Facts

ACTIVE INGREDIENT

Active ingredients | Purpose
OCTINOXATE 7.4% | Sunscreen
OCTOCRYLENE 3.0% | Sunscreen
TITANIUM DIOXIDE 4.6% | Sunscreen

Uses

- helps prevent sunburn
- if used as directed with other sun protection measures (see Directions), decreases the risk of skin cancer and early skin aging caused by the sun

Warnings

For external use only

Do not use on damaged or broken skin

When using this product keep out of eyes. Rinse with water to remove.

Stop use and ask a doctor if rash occurs

Keep out of reach of children. If product is swallowed, get medical help or contact a Poison Control Center right away.

Directions

- apply liberally 15 minutes before sun exposure
- use a water resistant sunscreen if swimming or sweating
- reapply at least every 2 hours
- Sun Protection Measures. Spending time in the sun increases your risk of skin cancer and early skin aging. To decrease this risk, regularly use a sunscreen with a broad spectrum SPF of 15 or higher and other sun protection measures including:
  - limit time in the sun, especially from 10 a.m. – 2 p.m.
  - wear long-sleeve shirts, pants, hats, and sunglasses
- children under 6 months: Ask a doctor

Inactive Ingredients

WATER•DIPROPYLENE GLYCOL•DIMETHICONE•ISOPROPYL MYRISTATE•GLYCERIN•CYCLOPENTASILOXANE•SD ALCOHOL 40-B•LAURYL PEG-9 POLYDIMETHYLSILOXYETHYL DIMETHICONE•METHYL METHACRYLATE CROSSPOLYMER•DISTEARDIMONIUM HECTORITE•POLYMETHYLSILSESQUIOXANE•PEG/PPG-14/7 DIMETHYL ETHER•CETYL PEG/PPG-10/1 DIMETHICONE•SILICA•SORBITAN SESQUIISOSTEARATE•TREHALOSE•DEXTRIN PALMITATE•TOCOPHERYL ACETATE•POLYQUATERNIUM-51•SODIUM ACETYLATED HYALURONATE•DIPOTASSIUM GLYCYRRHIZATE•SAXIFRAGA SARMENTOSA EXTRACT•GINKGO BILOBA LEAF EXTRACT•THYMUS SERPYLLUM EXTRACT•HYDROLYZED SILK•2-O-ETHYL ASCORBIC ACID•SCUTELLARIA BAICALENSIS ROOT EXTRACT•UNCARIA GAMBIR EXTRACT•GARCINIA MANGOSTANA BARK EXTRACT•HIBISCUS SABDARIFFA FLOWER EXTRACT•PANAX GINSENG ROOT EXTRACT•BUPLEURUM FALCATUM ROOT EXTRACT•HYDROLYZED CONCHIOLIN PROTEIN•PPG-17•HYDRATED SILICA•TRIETHOXYCAPRYLYLSILANE•BUTYLENE GLYCOL•TRISODIUM EDTA•ALUMINUM HYDROXIDE•POLYSILICONE-2•ALCOHOL•DISTEARYLDIMONIUM CHLORIDE•BHT•TOCOPHEROL•SODIUM METABISULFITE•TALC•THEANINE•METHYLPARABEN•PHENOXYETHANOL•FRAGRANCE•TITANIUM DIOXIDE•IRON OXIDES•MICA•

Other information

- protect this product in this container from excessive heat and direct sun.

Questions or comments?

Call toll free 1-800-906-7503

PRINCIPAL DISPLAY PANEL - 30 mL Tube Carton - IVORY

clé de peau
BEAUTÉ

50+

UV protective cream
tinted

BROAD SPECTRUM
SPF 50+
SUNSCREEN

30mL NET WT. 1.2 OZ.

PRINCIPAL DISPLAY PANEL - 30 mL Tube Carton - OCHER

clé de peau
BEAUTÉ

50+

UV protective cream
tinted

BROAD SPECTRUM
SPF 50+
SUNSCREEN

30mL NET WT. 1.2 OZ.

PRINCIPAL DISPLAY PANEL - 30 mL Tube Carton - DARK

clé de peau
BEAUTÉ

50+

UV protective cream
tinted

BROAD SPECTRUM
SPF 50+
SUNSCREEN

30mL NET WT. 1.2 OZ.